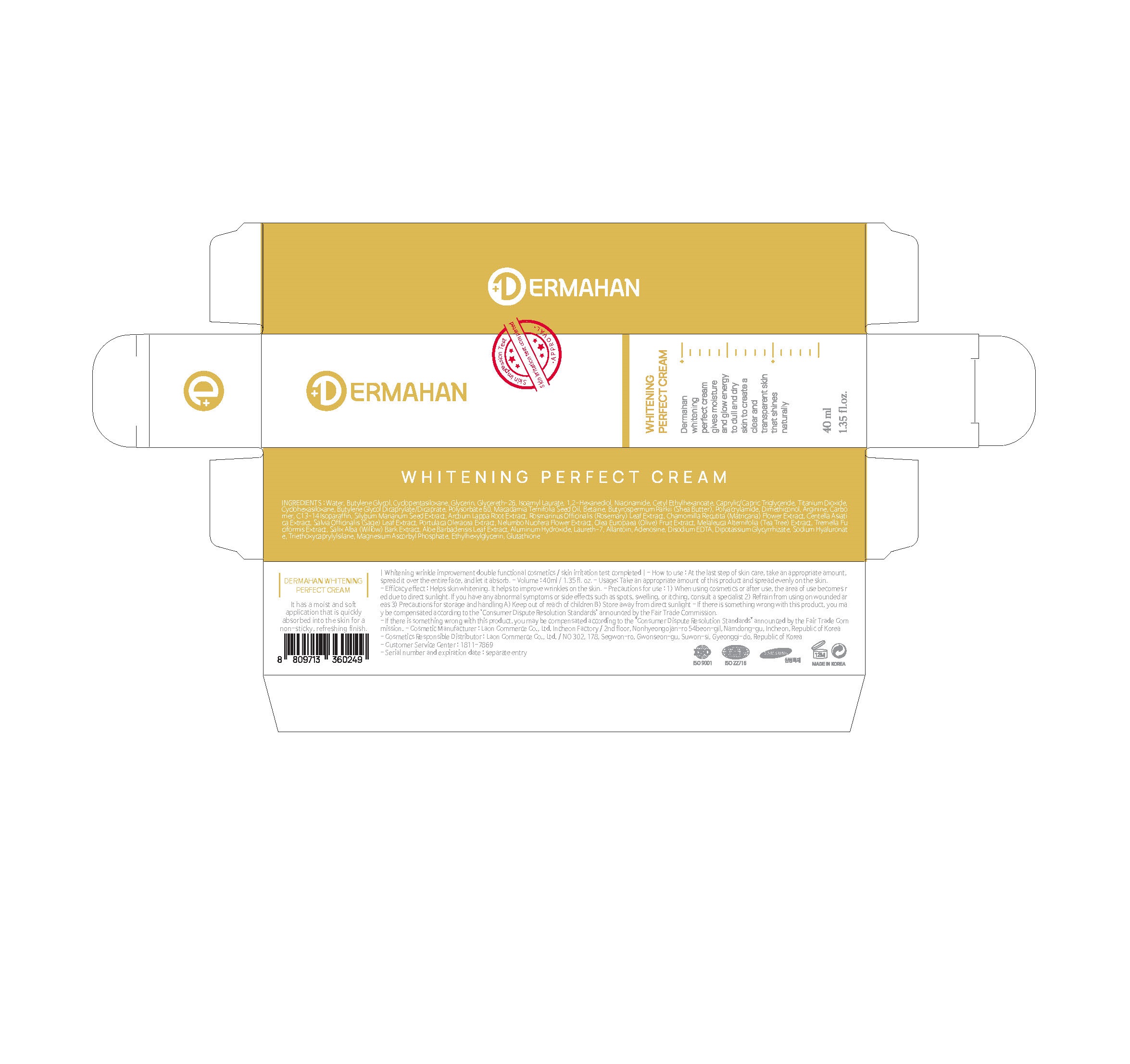 DRUG LABEL: DERMAHAN WHITENING PERFECTCREAM
NDC: 82083-0004 | Form: CREAM
Manufacturer: LAON COMMERCE co ltd
Category: otc | Type: HUMAN OTC DRUG LABEL
Date: 20211024

ACTIVE INGREDIENTS: NIACINAMIDE 2 g/100 mL; ADENOSINE 0.04 g/100 mL
INACTIVE INGREDIENTS: WATER

ACTIVE INGREDIENT

niacinamide,, adenosine

INACTIVE INGREDIENT

Water
Butylene Glycol
Cyclopentasiloxane
Glycerin
Glycereth-26
Isoamyl Laurate
1,2-Hexanediol
Cetyl Ethylhexanoate
Caprylic/Capric Triglyceride
Titanium Dioxide
Cyclohexasiloxane
Butylene Glycol Dicaprylate/Dicaprate
Polysorbate 60
Macadamia Ternifolia Seed Oil
Betaine
Butyrospermum Parkii (Shea Butter)
Polyacrylamide
Dimethiconol
Arginine
Carbomer
C13-14 Isoparaffin
Silybum Marianum Seed Extract
Arctium Lappa Root Extract
Rosmarinus Officinalis (Rosemary) Leaf Extract
Chamomilla Recutita (Matricaria) Flower Extract
Centella Asiatica Extract
Salvia Officinalis (Sage) Leaf Extract
Portulaca Oleracea Extract
Nelumbo Nucifera Flower Extract
Olea Europaea (Olive) Fruit Extract
Melaleuca Alternifolia (Tea Tree) Extract
Tremella Fuciformis Extract
Salix Alba (Willow) Bark Extract
Aloe Barbadensis Leaf Extract
Aluminum Hydroxide
Laureth-7
Allantoin
Disodium EDTA
Dipotassium Glycyrrhizate
Sodium Hyaluronate
Triethoxycaprylylsilane
Magnesium Ascorbyl Phosphate
Ethylhexylglycerin
Glutathione

PURPOSE

whitening wrinkle improvement

WARNINGS

■ if following abnormal symptoms persist, discontinue use

Irritation around the eyes, ears, mucous membranes, including the mouth, under the skin irritation and rashes

■ Stop immediately and consult a doctor if you experience

1) Hypersensitivity symptoms such as erythema, itching and dermatitis.

2) Skin Irritation

3) Following Instructions when using medication

(1) For external use only (Do not use internally)

(2) Avoid getting into the eyes (if contact occurs, wash well with clean water)

Keep Out of Reach of Children.

INDICATIONS AND USAGE

At the last step of skin care, take an appropriate amount,

spread it over the entire face, and let it absorb.

DOSAGE AND ADMINISTRATION

for external use only